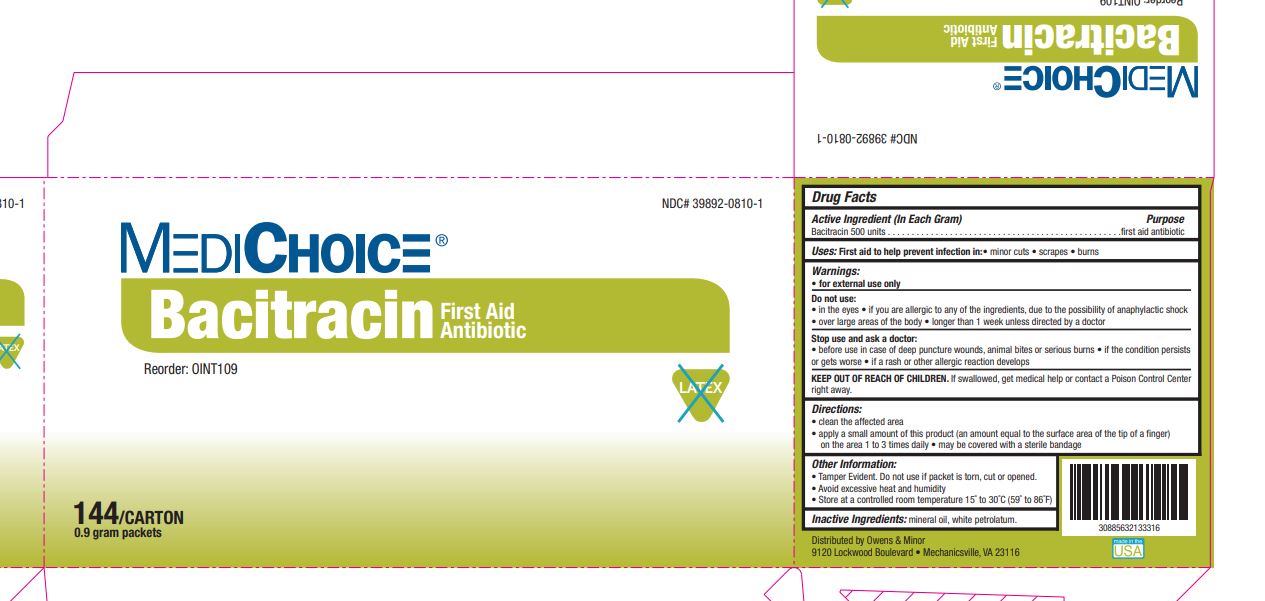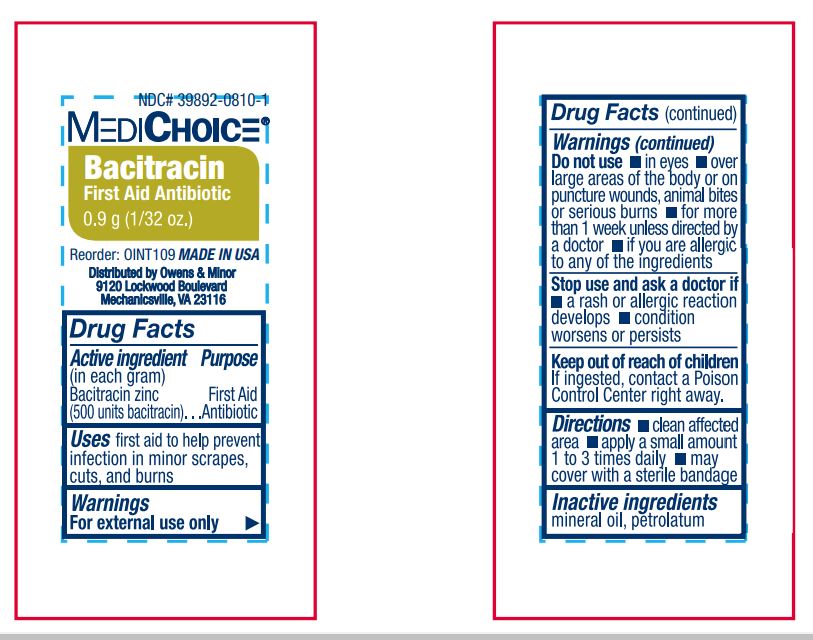 DRUG LABEL: MediChoice Bacitracin
NDC: 39892-0810 | Form: OINTMENT
Manufacturer: O&M HALYARD, INC.
Category: otc | Type: HUMAN OTC DRUG LABEL
Date: 20251009

ACTIVE INGREDIENTS: BACITRACIN 500 [iU]/1 g
INACTIVE INGREDIENTS: PETROLATUM

MediChoice Bacitracin

Active Ingredient (In Each Gram)

Bacitracin 500 units

Purpose

First aid antibiotic

Uses

First aid to help prevent infection in: • minor cuts • scrapes • burns

Warnings

• for external use only

Do not use:

• in the eyes • if you are allergic to any of the ingredients, due to the possibility of anaphylactic shock • over large areas of the body • longer than 1 week unless directed by a doctor

Stop use and ask a doctor:

• before use in case of deep puncture wounds, animal bites or serious burns • if the condition persists or gets worse • if a rash or other allergic reaction develops

KEEP OUT OF REACH OF CHILDREN.

If swallowed, get medical help or contact a Poison Control Center right away.

Directions

• clean the affected area • apply a small amount of this product (an amount equal to the surface area of the tip of a finger) on the area 1 to 3 times daily • may be covered with a sterile bandage

Other Information:

• Tamper Evident. Do not use if package is torn, cut or opened. • Avoid excessive heat and humidity • Store at a controlled room temperature 15˚ to 30˚C (59˚ to 86˚F)

Inactive Ingredients

white petrolatum.